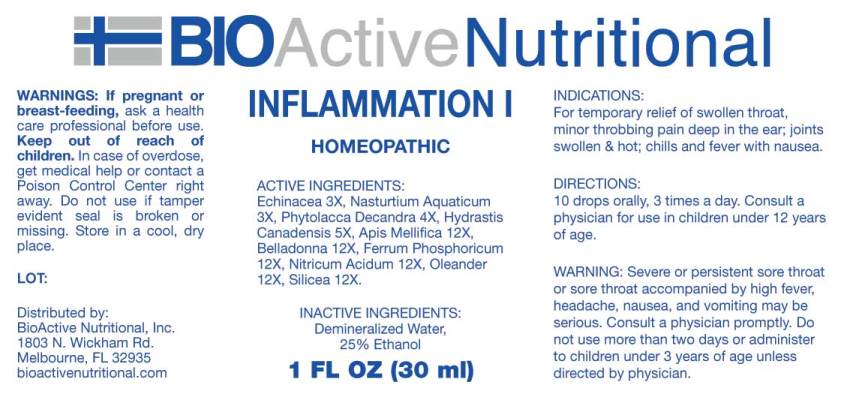 DRUG LABEL: Inflammation
NDC: 43857-0470 | Form: LIQUID
Manufacturer: BioActive Nutritional, Inc.
Category: homeopathic | Type: HUMAN OTC DRUG LABEL
Date: 20250519

ACTIVE INGREDIENTS: ECHINACEA ANGUSTIFOLIA WHOLE 3 [hp_X]/1 mL; NASTURTIUM OFFICINALE 3 [hp_X]/1 mL; PHYTOLACCA AMERICANA ROOT 4 [hp_X]/1 mL; GOLDENSEAL 5 [hp_X]/1 mL; APIS MELLIFERA 12 [hp_X]/1 mL; ATROPA BELLADONNA 12 [hp_X]/1 mL; FERROSOFERRIC PHOSPHATE 12 [hp_X]/1 mL; NITRIC ACID 12 [hp_X]/1 mL; NERIUM OLEANDER LEAF 12 [hp_X]/1 mL; SILICON DIOXIDE 12 [hp_X]/1 mL
INACTIVE INGREDIENTS: WATER; ALCOHOL

Drug Facts:

ACTIVE INGREDIENTS:

Echinacea (Angustifolia) 3X, Nasturtium Aquaticum 3X, Phytolacca Decandra 4X, Hydrastis Canadensis 5X, Apis Mellifica 12X, Belladonna 12X, Ferrum Phosphoricum 12X, Nitricum Acidum 12X, Oleander 12X, Silicea 12X.

INDICATIONS:

For temporary relief of swollen throat, minor throbbing pain deep in the ear; joints swollen and hot; chills and fever with nausea.

WARNINGS:

If pregnant or breast-feeding, ask a health care professional before use.

Keep out of reach of children. In case of overdose, get medical help or contact a Poison Control Center right away.

Do not use if tamper evident seal is broken or missing.

Store in cool, dry place.

WARNING: Severe or persistent sore throat or sore throat accompanied by high fever, headache, nausea, and vomiting may be serious. Consult a physician promptly. Do not use more than two days or administer to children under 3 years of age unless directed by physician.

Keep out of reach of children. In case of overdose, get medical help or contact a Poison Control Center right away.

DIRECTIONS:

10 drops orally, 3 times a day. Consult a physician for use in children under 12 years of age.

INDICATIONS:

For temporary relief of swollen throat, minor throbbing pain deep in the ear; joints swollen and hot; chills and fever with nausea.

INACTIVE INGREDIENTS:

Demineralized Water, 25% Ethanol.

QUESTIONS:

Distributed by:

BioActive Nutritional, Inc.

1803 N. Wickham Rd.

Melbourne, FL 32935

bioactivenutritional.com

PACKAGE LABEL DISPLAY:

BIOActive Nutritional

INFLAMMATION I

HOMEOPATHIC

1 FL OZ (30 ml)